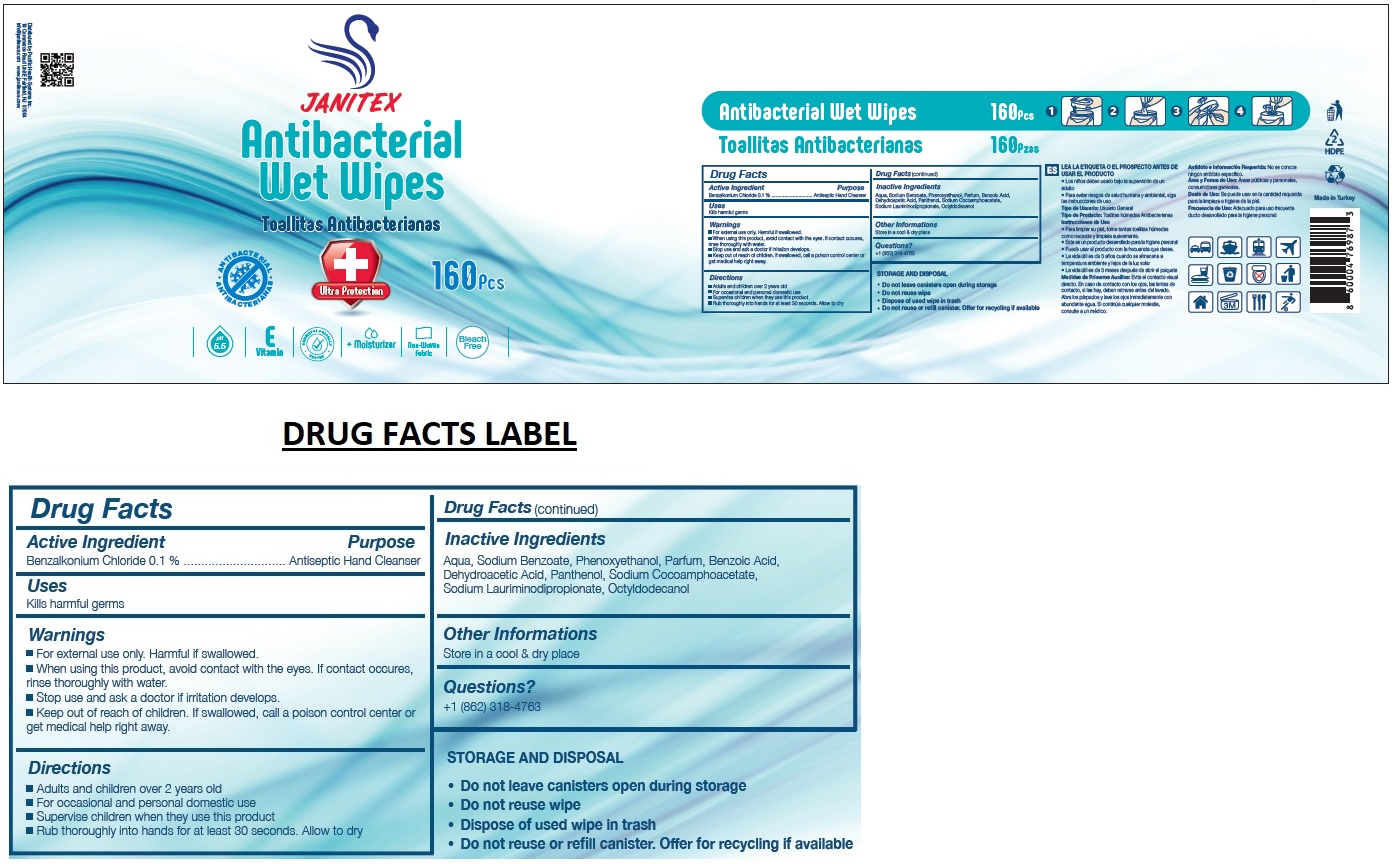 DRUG LABEL: JANITEX ANTIBACTERIAL WET WIPES
NDC: 79519-021 | Form: CLOTH
Manufacturer: Pacific Health Systems Inc.
Category: otc | Type: HUMAN OTC DRUG LABEL
Date: 20200918

ACTIVE INGREDIENTS: BENZALKONIUM CHLORIDE 0.1 g/100 g
INACTIVE INGREDIENTS: WATER; SODIUM BENZOATE; PHENOXYETHANOL; BENZOIC ACID; DEHYDROACETIC ACID; PANTHENOL; SODIUM COCOAMPHOACETATE; SODIUM LAURIMINODIPROPIONATE; OCTYLDODECANOL

JANITEX Antibacterial Wet Wipes

Active Ingredient

Benzalkonium Chloride 0.1 %

Purpose

Antiseptic Hand Cleanser

Uses

Kills harmful germs

Warnings

• For external use only. Harmful if swallowed.
• When using this product, avoid contact with the eyes. If contact occurs, rinse thoroughly with water.
• Stop use and ask a doctor if irritation develops.

• Keep out of reach of children. If swallowed, call a poison control center or get medical help right away.

Directions

• Adults and children over 2 years old
• For occasional and personal domestic use
• Supervise children when they use this product
• Rub thoroughly into hands for at least 30 seconds. Allow to dry

Inactive Ingredients

Aqua, Sodium Benzoate, Phenoxyethanol, Parfum, Benzoic Acid, Dehydroacetic Acid, Panthenol, Sodium Cocoamphoacetate, Sodium Lauriminodipropionate, Octyldodecanol

Other Informations

Store in a cool & dry place

Questions?

+1 (862) 318-4763

ANTIBACTERIAL

Ultra Protection

pH 5.5

E Vitamin

DERMATOLOGICALLY TESTED

+ Moisturizer

Non-Woven Fabric

Bleach Free

Distributed by Pacific Health Systems Inc.

19 Commerce Road Unit E Fairfield, NJ 07004

info@janitexus.com www.janitexus.com

STORAGE AND DISPOSAL

• Do not leave canisters open during storage

• Do not reuse wipe

• Dispose of used wipe in trash

• Do not reuse or refill canister. Offer for recycling if available

Made in Turkey